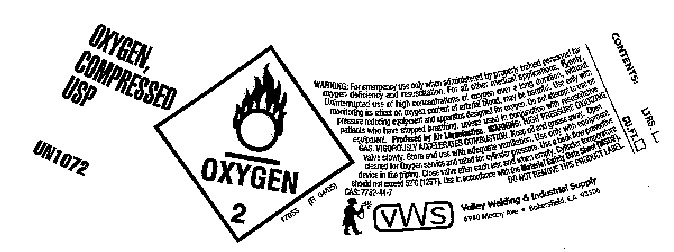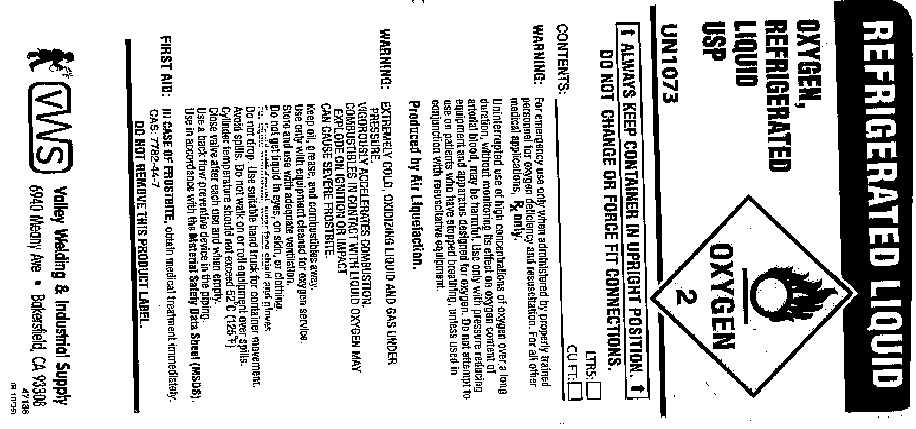 DRUG LABEL: Oxygen
NDC: 42924-001 | Form: GAS
Manufacturer: Terjan Co., Inc. DBA Valley Welding Supply Company
Category: prescription | Type: HUMAN PRESCRIPTION DRUG LABEL
Date: 20100330

ACTIVE INGREDIENTS: Oxygen 990 mL/1 L

oxygen

PACKAGE LABEL

OXYGEN,
COMPRESSED
USP
U.N. 1072
OXYGEN 2
17055 (R 04/35)
WARNING: For emergency use only when administered by properly trained personnel for oxygen deficiency and resuscitation. For all other medical applications, RX ONLY.
Uninterrupted use of high concentrations of oxygen over a long duration, without monitoring its effect on oxygen content of arterial blood, may be harmful. Use only with pressure reducing equipment and apparatus designed for oxygen. Do not attempt to use on patients who have stopped breathing, unless used in conjunction with resuscitative equipment. PRODUCED BY AIR LIQUEFACTION. WARNING: HIGH PRESSURE OXIDIZING GAS. VIGOROUSLY ACCELERATES COMBUSTION. Keep oil and grease away. Open valve slowly. Store and use with adequate ventilation. Use only with equipment cleaned for oxygen service and rated for cylinder pressure. Use a back flow preventive device in the piping. Close valve after each use and when empty. Cylinder temperature should not exceed 52 degrees C (125 degrees F). Use in accordance with the Material Data Safety Sheet (MSDS).
CAS 7782-44-7
DO NOT REMOVE THIS LABEL
Valley Welding and Industrial Supply
6940 Meany Ave. Bakersfield, CA 93308
Contents: LTRS:
CU.FT

PACKAGE LABEL

REFRIGERATED LIQUID
OXYGEN,
Refrigerated
Liquid
USP
UN 1073
OXYGEN 2
ALWAYS KEEP CONTAINER IN UPRIGHT POSITION.
DO NOT CHANGE OR FORCE FIT CONNECTIONS.
CONTENTS: LTRS: CUFT:
For emergency use only when administered by properly trained personnel for oxygen deficiency and resuscitation. For all other medical applications, Rx ONLY.
Uninterrupted use of high concentrations of oxygen over a long duration, without monitoring its effect on oxygen content of arterial blood, may be harmful. Use only with pressure reducing equipment and apparatus designed for oxygen. Do not attempt to use on patients who have stopped breathing, unless used in conjunction with resuscitative equipment.
Produced by Air Liquefaction.
WARNING: EXTREMELY COLD OXIDIZING LIQUID AND GAS UNDER PRESSURE.
VIGOROUSLY ACCELERATES COMBUSTION.
COMBUSTIBLES IN CONTACT WITH LIQUID OXYGEN MAY EXPLODE ON IGNITION OR IMPACT.
CAN CAUSE SEVERE FROSTBITE.
Keep oil, grease and combustibles away.
Use only with equipment cleaned for oxygen service.
Store and use with adequate ventilation.
Do not get liquid in eyes, on skin or clothing.
For liquid withdrawal, wear face shield and gloves.
Do not drop. Use suitable hand truck for container movement.
Avoid spills. Do not walk on or roll equipment over spills.
Cylinder temperature should not exceed 52 degrees C (125 degrees F).
Close valve after each use and when empty.
Use a back flow preventive device in the piping.
Use in accordance with the Material Data Safety Sheet (MSDS).
FIRST AID: IN CASE OF FROSTBITE, obtain medical treatment immediately.
CAS 7782-44-7
DO NOT REMOVE THIS PRODUCT LABEL.
Valley Welding and Industrial Supply
6940 Meany Ave. Bakersfield, CA 93308